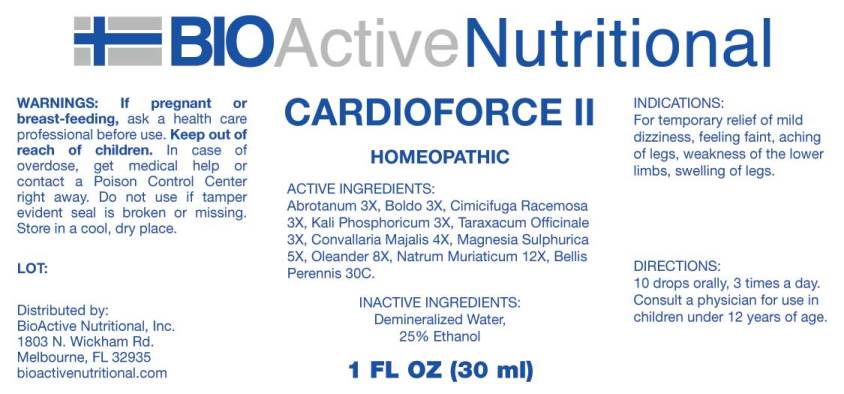 DRUG LABEL: Cardioforce
NDC: 43857-0437 | Form: LIQUID
Manufacturer: BioActive Nutritional, Inc.
Category: homeopathic | Type: HUMAN OTC DRUG LABEL
Date: 20170302

ACTIVE INGREDIENTS: ARTEMISIA ABROTANUM FLOWERING TOP 3 [hp_X]/1 mL; PEUMUS BOLDUS LEAF 3 [hp_X]/1 mL; BLACK COHOSH 3 [hp_X]/1 mL; POTASSIUM PHOSPHATE, DIBASIC 3 [hp_X]/1 mL; TARAXACUM OFFICINALE 3 [hp_X]/1 mL; CONVALLARIA MAJALIS 4 [hp_X]/1 mL; MAGNESIUM SULFATE HEPTAHYDRATE 5 [hp_X]/1 mL; NERIUM OLEANDER LEAF 8 [hp_X]/1 mL; SODIUM CHLORIDE 12 [hp_X]/1 mL; BELLIS PERENNIS 30 [hp_C]/1 mL
INACTIVE INGREDIENTS: WATER; ALCOHOL

Drug Facts:

ACTIVE INGREDIENTS:

Abrotanum 3X, Boldo 3X, Cimicifuga Racemosa 3X, Kali Phosphoricum 3X, Taraxacum Officinale 3X, Convallaria Majalis 4X, Magnesia Sulphurica 5X, Oleander 8X, Natrum Muriaticum 12X, Bellis Perennis 30C.

INDICATIONS:

For temporary relief of mild dizziness, feeling faint, aching of legs, weakness of the lower limbs, swelling of legs.

WARNINGS:

If pregnant or breast-feeding, ask a health care professional before use.

Keep out of reach of children. In case of overdose, get medical help or contact a Poison Control Center right away.

Do not use if tamper evident seal is broken or missing.

Store in cool, dry place.

Keep out of reach of children. In case of overdose, get medical help or contact a Poison Control Center right away.

DIRECTIONS:

10 drops orally, 3 times a day. Consult a physician for use in children under 12 years of age.

INDICATIONS:

For temporary relief of mild dizziness, feeling faint, aching of legs, weakness of the lower limbs, swelling of legs.

INACTIVE INGREDIENTS:

Demineralized Water, 25% Ethanol

QUESTIONS:

Distributed by:

BioActive Nutritional, Inc.

1803 N. Wickham Rd.

Melbourne, FL 32935

bioactivenutritional.com

PACKAGE LABEL DISPLAY:

BioActive Homeopathic

CARDIOFORCE II

1 FL OZ (30 ml)